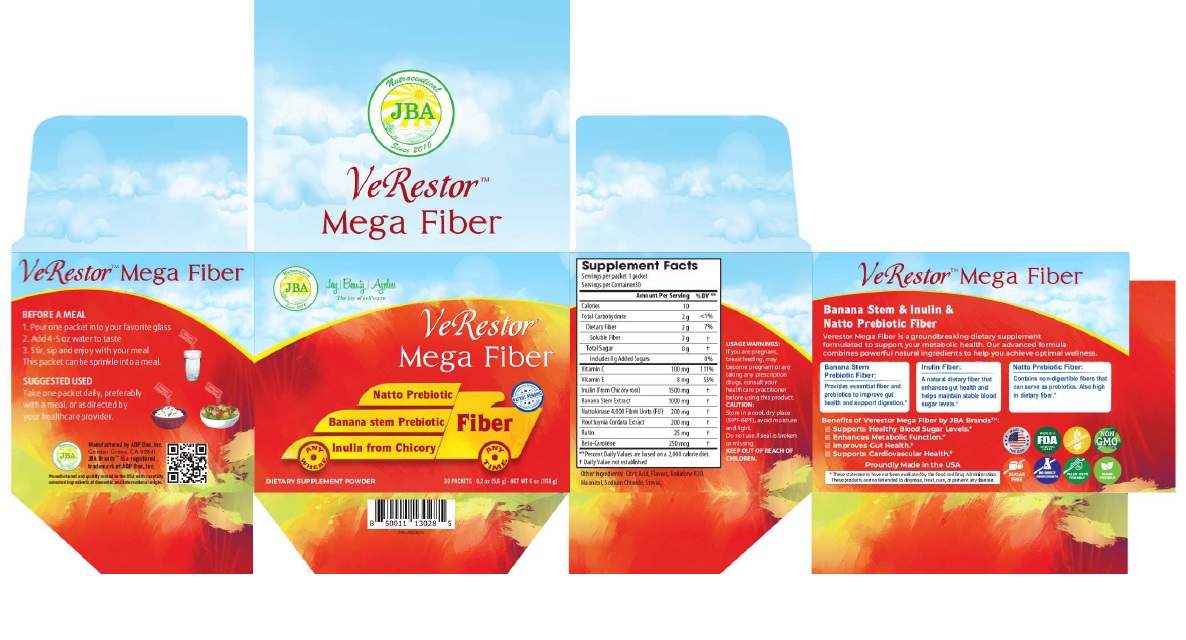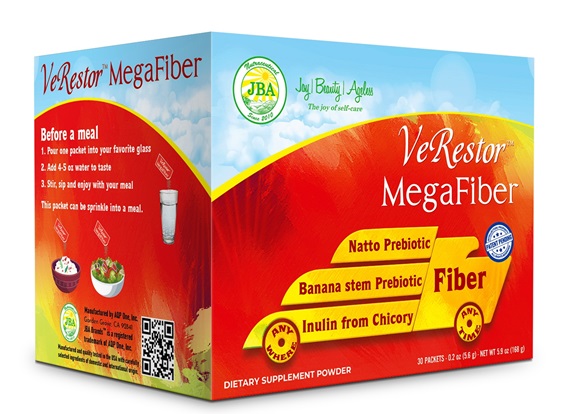 DRUG LABEL: JBA Verestor Mega Fiber Powder
NDC: 13411-862 | Form: POWDER
Manufacturer: Advanced Pharmaceutical Services, Inc. Dba Affordable Quality Pharmaceuticals
Category: otc | Type: HUMAN OTC DRUG LABEL
Date: 20251128

ACTIVE INGREDIENTS: ASCORBIC ACID 100 mg/1 1; .ALPHA.-TOCOPHEROL 8 mg/1 1; INULIN 1500 mg/1 1; BANANA 1000 mg/1 1; NATTOKINASE 200 mg/1 1; HOUTTUYNIA CORDATA TOP 200 mg/1 1; RUTIN 25 mg/1 1; BETA CAROTENE 250 ug/1 1
INACTIVE INGREDIENTS: ANHYDROUS CITRIC ACID; POVIDONE K30; MANNITOL; SODIUM CHLORIDE; STEVIOSIDE

Identity

Dietary supplement

Direction

Take one packet daily, preferably with a meal, or as directed by your healthcare provider.

Safe handling warning

VERESTORTMMega Fiber

Banana Stem & Inulin & Natto Prebiotic Fiber

VerestorTMMega Fiber is a groundbreaking dietary supplement formulated to support your metabolic health. Our advanced formula combines powerful natural ingredients to help you achieve optimal wellness.

Banana Stem Prebiotic Fiber:
Provides essential fiber and prebiotics to improve gut health and support digestion.*

Inulin Fiber:
A natural dietary fiber that enhances gut health and helps maintain stable blood sugar levels.*

Natto Prebiotic Fiber:
Contains non-digestible fibers that can serve as prebiotic. Also high in dietary fiber.

Benefits of Verestor Mega Fiber by JBA Brands:

- Supports Healthy Blood Sugar Levels*
- Enhances Metabolic Function*
- Improves Gut Health*
- Supports Cardiovascular Health*

* These statements have not been evaluated by the Food & Drug Administration. This product is not intended to diagnose, treat, cure, or prevent any disease.

PRECAUTIONS

If you are pregnant, breastfeeding, may become pregnant or are taking any prescription drugs, consult your healthcare professional before using this product.

Keep Out of The Reach of Children. Store in a cool, dry place (59oF-86oF), avoid moisture and light.

WARNINGS

Other Ingredients

Citric Acid, Kollidone, Mannitol, Sodium Chloride, Stevia